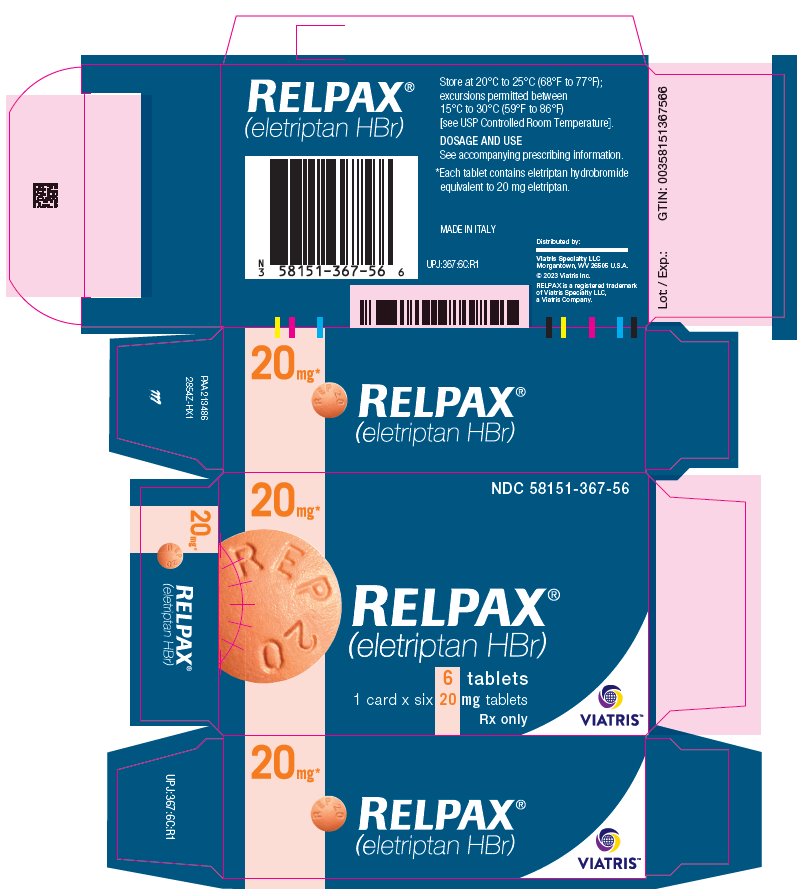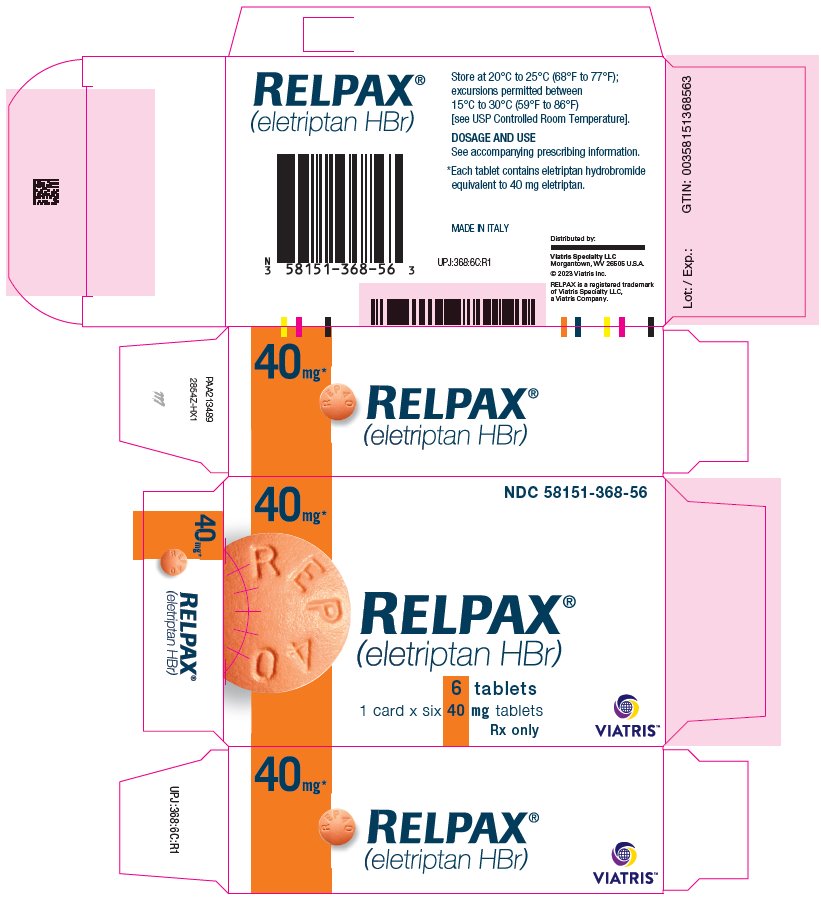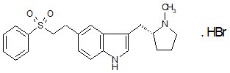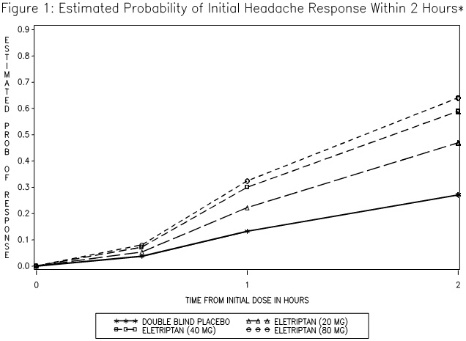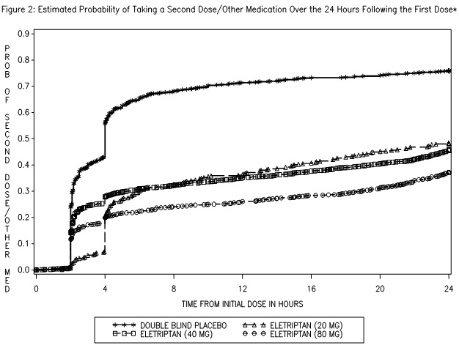 DRUG LABEL: Relpax
NDC: 58151-367 | Form: TABLET
Manufacturer: Viatris Specialty LLC
Category: prescription | Type: HUMAN PRESCRIPTION DRUG LABEL
Date: 20240115

ACTIVE INGREDIENTS: ELETRIPTAN HYDROBROMIDE 20 mg/1 1
INACTIVE INGREDIENTS: CROSCARMELLOSE SODIUM; FD&C YELLOW NO. 6; HYPROMELLOSE, UNSPECIFIED; LACTOSE MONOHYDRATE; MAGNESIUM STEARATE; MICROCRYSTALLINE CELLULOSE; TITANIUM DIOXIDE; TRIACETIN

HIGHLIGHTS OF PRESCRIBING INFORMATION

These highlights do not include all the information needed to use RELPAX safely and effectively. See full prescribing information for RELPAX.
RELPAX® (eletriptan hydrobromide) tablets, for oral use
Initial U.S. Approval: 2002

1 INDICATIONS AND USAGE

RELPAX is a serotonin (5-HT1B/1D) receptor agonist (triptan) indicated for the acute treatment of migraine with or without aura in adults (1)

Limitations of Use:

- Use only after a clear diagnosis of migraine has been established (1)
- Not indicated for the prophylactic therapy of migraine (1)
- Not indicated for the treatment of cluster headache (1)

2 DOSAGE AND ADMINISTRATION

- Single dose: 20 mg or 40 mg (2)
- Maximum single dose: 40 mg (2)
- May repeat dose after 2 hours if needed; not to exceed 80 mg in any 24-hour period (2)

3 DOSAGE FORMS AND STRENGTHS

Tablets: 20 mg and 40 mg (3)

4 CONTRAINDICATIONS

- History of coronary artery disease (CAD) or coronary artery vasospasm (4)
- Wolff-Parkinson-White syndrome or other cardiac accessory conduction pathway disorders (4)
- History of stroke, transient ischemic attack, or history or current evidence of hemiplegic or basilar migraine (4)
- Peripheral vascular disease (4)
- Ischemic bowel disease (4)
- Uncontrolled hypertension (4)
- Within 24 hours of treatment with another 5-HT1 agonist, or an ergotamine-containing medication (4)
- Hypersensitivity to RELPAX (angioedema and anaphylaxis seen) (4)
- Within at least 72 hours of treatment with the following potent CYP3A4 inhibitors: ketoconazole, itraconazole, nefazodone, troleandomycin, clarithromycin, ritonavir, or nelfinavir (4)

5 WARNINGS AND PRECAUTIONS

- Myocardial ischemia/infarction or Prinzmetal's angina: Perform cardiac evaluation in patients with multiple cardiovascular risk factors (5.1)
- Arrhythmias: Discontinue RELPAX if occurs (5.2)
- Chest/throat/neck/jaw pain, tightness, pressure, or heaviness: Generally not myocardial ischemia; evaluate high risk patients for CAD (5.3)
- Cerebral hemorrhage, subarachnoid hemorrhage, or stroke: Discontinue RELPAX if occurs (5.4)
- Gastrointestinal ischemia or infarction events, or peripheral vasospastic reactions: Discontinue RELPAX if occurs (5.5)
- Medication overuse headache: Detoxification may be necessary (5.6)
- Serotonin syndrome: Discontinue RELPAX if occurs (5.7, 7.3)

6 ADVERSE REACTIONS

Most common adverse reactions (≥ 5% and > placebo) were asthenia, nausea, dizziness, and somnolence. These reactions appear to be dose-related. (6.1)

To report SUSPECTED ADVERSE REACTIONS, contact Viatris at 1-877-446-3679 (1-877-4-INFO-RX) or FDA at 1-800-FDA-1088 or www.fda.gov/medwatch.

8 USE IN SPECIFIC POPULATIONS

Pregnancy: Based on animal data, may cause fetal harm (8.1)

FULL PRESCRIBING INFORMATION

1 INDICATIONS AND USAGE

RELPAX is indicated for the acute treatment of migraine with or without aura in adults.

Limitations of Use:

- Use only if a clear diagnosis of migraine has been established. If a patient has no response to the first migraine attack treated with RELPAX, reconsider the diagnosis of migraine before RELPAX is administered to treat any subsequent attacks.
- RELPAX is not intended for the prevention of migraine attacks.
- Safety and effectiveness of RELPAX have not been established for cluster headache.

2 DOSAGE AND ADMINISTRATION

The maximum recommended single dose is 40 mg.

In controlled clinical trials, single doses of 20 mg and 40 mg were effective for the acute treatment of migraine in adults. A greater proportion of patients had a response following a 40 mg dose than following a 20 mg dose [see Clinical Studies (14)].

If the migraine has not resolved by 2 hours after taking RELPAX, or returns after transient improvement, a second dose may be administered at least 2 hours after the first dose. The maximum daily dose should not exceed 80 mg.

The safety of treating an average of more than 3 migraine attacks in a 30-day period has not been established.

3 DOSAGE FORMS AND STRENGTHS

20 mg Tablets: Orange, round, convex shaped, film-coated, debossed with “REP 20” on one side and “VLE” on the other side.

40 mg Tablets: Orange, round, convex shaped, film-coated, debossed with “REP 40” on one side and “VLE” on the other side.

4 CONTRAINDICATIONS

RELPAX is contraindicated in patients with:

- Ischemic coronary artery disease (CAD) (angina pectoris, history of myocardial infarction, or documented silent ischemia) or coronary artery vasospasm, including Prinzmetal's angina [see Warnings and Precautions (5.1)].
- Wolff-Parkinson-White syndrome or arrhythmias associated with other cardiac accessory conduction pathway disorders [see Warnings and Precautions (5.2)].
- History of stroke, transient ischemic attack (TIA), or history or current evidence of hemiplegic or basilar migraine because these patients are at a higher risk of stroke [see Warnings and Precautions (5.4)].
- Peripheral vascular disease [see Warnings and Precautions (5.5)].
- Ischemic bowel disease [see Warnings and Precautions (5.5)].
- Uncontrolled hypertension [see Warnings and Precautions (5.8)].
- Recent use (i.e., within 24 hours) of another 5-hydroxytryptamine1 (5-HT1) agonist, ergotamine-containing medication, or ergot-type medication such as dihydroergotamine (DHE) or methysergide [see Drug Interactions (7.1)].
- Hypersensitivity to RELPAX (angioedema and anaphylaxis seen) [see Warnings and Precautions (5.9)].
- Recent use (i.e., within at least 72 hours) of the following potent CYP3A4 inhibitors: ketoconazole, itraconazole, nefazodone, troleandomycin, clarithromycin, ritonavir, or nelfinavir [see Drug Interactions (7.2) and Clinical Pharmacology (12.3)].

5 WARNINGS AND PRECAUTIONS

RELPAX should only be used where a clear diagnosis of migraine has been established.

5.1 Myocardial Ischemia, Myocardial Infarction, and Prinzmetal's Angina

RELPAX is contraindicated in patients with ischemic or vasospastic CAD. There have been rare reports of serious cardiac adverse reactions, including acute myocardial infarction, occurring within a few hours following administration of RELPAX. Some of these reactions occurred in patients without known CAD. RELPAX may cause coronary artery vasospasm (Prinzmetal's angina), even in patients without a history of CAD.

Perform a cardiovascular evaluation in triptan-naïve patients who have multiple cardiovascular risk factors (e.g., increased age, diabetes, hypertension, smoking, obesity, strong family history of CAD) prior to receiving RELPAX. Do not use RELPAX if there is evidence of CAD or coronary artery vasospasm [see Contraindications (4)]. For patients with multiple cardiovascular risk factors who have a negative cardiovascular evaluation, consider administering the first RELPAX dose in a medically-supervised setting and performing an electrocardiogram (ECG) immediately following administration of RELPAX. For such patients, consider periodic cardiovascular evaluation in intermittent long-term users of RELPAX.

5.2 Arrhythmias

Life-threatening disturbances of cardiac rhythm including ventricular tachycardia and ventricular fibrillation leading to death have been reported within a few hours following the administration of 5-HT1 agonists. Discontinue RELPAX if these disturbances occur. RELPAX is contraindicated in patients with Wolff-Parkinson-White syndrome or arrhythmias associated with other cardiac accessory conduction pathway disorders [see Contraindications (4)].

5.3 Chest, Throat, Neck and/or Jaw Pain/Tightness/Pressure

Sensations of tightness, pain, and pressure in the chest, throat, neck, and jaw commonly occur after treatment with RELPAX and are usually non-cardiac in origin. However, perform a cardiac evaluation if these patients are at high cardiac risk. RELPAX is contraindicated in patients with CAD or Prinzmetal's variant angina [see Contraindications (4)].

5.4 Cerebrovascular Events

Cerebral hemorrhage, subarachnoid hemorrhage, and stroke have occurred in patients treated with 5-HT1 agonists, and some have resulted in fatalities. In a number of cases, it appears possible that the cerebrovascular events were primary, the 5-HT1 agonist having been administered in the incorrect belief that the symptoms experienced were a consequence of migraine, when they were not.

Before treating headaches in patients not previously diagnosed as migraineurs, and in migraineurs who present with symptoms atypical of migraine, other potentially serious neurological conditions need to be excluded. RELPAX is contraindicated in patients with a history of stroke or TIA [see Contraindications (4)].

5.5 Other Vasospasm Reactions

RELPAX may cause non-coronary vasospastic reactions, such as peripheral vascular ischemia, gastrointestinal vascular ischemia and infarction (presenting with abdominal pain and bloody diarrhea), and Raynaud's syndrome. In patients who experience symptoms or signs suggestive of a vasospastic reaction following the use of any 5-HT1 agonist, rule out a vasospastic reaction before receiving additional RELPAX doses [see Contraindications (4)].

5.6 Medication Overuse Headache

Overuse of acute migraine drugs (e.g., ergotamine, triptans, opioids, or combination of these drugs for 10 or more days per month) may lead to exacerbation of headache (medication overuse headache). Medication overuse headache may present as migraine-like daily headaches or as a marked increase in frequency of migraine attacks. Detoxification of patients, including withdrawal of the overused acute migraine drugs and treatment of withdrawal symptoms (which often includes a transient worsening of headache) may be necessary.

5.7 Serotonin Syndrome

Serotonin syndrome may occur with RELPAX, particularly during co-administration with selective serotonin reuptake inhibitors (SSRIs), serotonin and norepinephrine reuptake inhibitors (SNRIs), tricyclic antidepressants (TCAs), and monoamine oxidase (MAO) inhibitors [see Drug Interactions (7.3)]. Serotonin syndrome symptoms may include mental status changes (e.g., agitation, hallucinations, coma), autonomic instability (e.g., tachycardia, labile blood pressure, hyperthermia), neuromuscular aberrations (e.g., hyperreflexia, incoordination), and/or gastrointestinal symptoms (e.g., nausea, vomiting, diarrhea). The onset of symptoms usually occurs within minutes to hours of receiving a new or a greater dose of a serotonergic medication. Discontinue RELPAX if serotonin syndrome is suspected.

5.8 Increase in Blood Pressure

Significant elevation in blood pressure, including hypertensive crisis with acute impairment of organ systems, has been reported on rare occasions in patients treated with 5-HT1 agonists, including patients without a history of hypertension. Monitor blood pressure in patients treated with RELPAX. RELPAX is contraindicated in patients with uncontrolled hypertension [see Contraindications (4)].

5.9 Anaphylactic/Anaphylactoid Reactions

There have been reports of anaphylaxis, anaphylactoid, and hypersensitivity reactions including angioedema in patients receiving RELPAX. Such reactions can be life-threatening or fatal. In general, anaphylactic reactions to drugs are more likely to occur in individuals with a history of sensitivity to multiple allergens. RELPAX is contraindicated in patients with a history of hypersensitivity reaction to RELPAX [see Contraindications (4)].

6 ADVERSE REACTIONS

The following adverse reactions are described elsewhere in other sections of the prescribing information:

- Myocardial ischemia and myocardial infarction, and Prinzmetal's angina [see Warnings and Precautions (5.2)]
- Arrhythmias [see Warnings and Precautions (5.3)]
- Chest, throat, neck, and/or jaw pain/tightness/pressure [see Warnings and Precautions (5.4)]
- Cerebrovascular events [see Warnings and Precautions (5.4)]
- Other vasospasm reactions [see Warnings and Precautions (5.5)]
- Medication overuse headache [see Warnings and Precautions (5.6)]
- Serotonin syndrome [see Warnings and Precautions (5.7)]
- Increase in blood pressure [see Warnings and Precautions (5.8)]
- Hypersensitivity reactions [see Contraindications (4) and Warnings and Precautions (5.9)]

6.1 Clinical Trials Experience

Because clinical studies are conducted under widely varying conditions, adverse reaction rates observed in the clinical studies of a drug cannot be directly compared to rates in the clinical studies of another drug and may not reflect the rates observed in practice.

Among 4,597 patients who treated the first migraine headache with RELPAX in short-term placebo-controlled trials, the most common adverse reactions reported with treatment with RELPAX were asthenia, nausea, dizziness, and somnolence. These reactions appear to be dose-related.

In long-term open-label studies where patients were allowed to treat multiple migraine attacks for up to 1 year, 128 (8.3%) out of 1,544 patients discontinued treatment due to adverse reactions.

Table 1 lists adverse reactions that occurred in the subset of 5,125 migraineurs who received eletriptan doses of 20 mg, 40 mg and 80 mg or placebo in worldwide placebo-controlled clinical trials.

Only adverse reactions that were more frequent in a RELPAX treatment group compared to the placebo group with an incidence greater than or equal to 2% are included in Table 1.

Table 1: Adverse Reactions Incidence in Placebo-Controlled Migraine Clinical Trials: Reactions Reported by ≥ 2% Patients Treated with RELPAX and More Than Placebo
Adverse Reaction Type | Placebo (n=988) | RELPAX 20 mg (n=431) | RELPAX 40 mg (n=1774) | RELPAX 80 mg (n=1932)
ATYPICAL SENSATIONS
Paresthesia | 2% | 3% | 3% | 4%
Flushing/feeling of warmth | 2% | 2% | 2% | 2%
PAIN AND PRESSURE SENSATIONS
Chest – tightness/pain/pressure | 1% | 1% | 2% | 4%
Abdominal – pain/discomfort/stomach pain/ cramps/pressure | 1% | 1% | 2% | 2%
DIGESTIVE
Dry mouth | 2% | 2% | 3% | 4%
Dyspepsia | 1% | 1% | 2% | 2%
Dysphagia – throat tightness/difficulty swallowing | 0.2% | 1% | 2% | 2%
Nausea | 5% | 4% | 5% | 8%
NEUROLOGICAL
Dizziness | 3% | 3% | 6% | 7%
Somnolence | 4% | 3% | 6% | 7%
Headache | 3% | 4% | 3% | 4%
OTHER
Asthenia | 3% | 4% | 5% | 10%

The frequency of adverse reactions in clinical trials did not increase when up to 2 doses of RELPAX were taken within 24 hours. The incidence of adverse reactions in controlled clinical trials was not affected by gender, age, or race of the patients. Adverse reaction frequencies were also unchanged by concomitant use of drugs commonly taken for migraine prophylaxis (e.g., SSRIs, beta blockers, calcium channel blockers, tricyclic antidepressants), estrogen replacement therapy or oral contraceptives.

6.2 Postmarketing Experience

The following adverse reaction(s) have been identified during post approval use of RELPAX. Because these reactions are reported voluntarily from a population of uncertain size, it is not always possible to reliably estimate their frequency or establish a causal relationship to drug exposure.

Neurological: seizure

Digestive: vomiting

7 DRUG INTERACTIONS

7.1 Ergot-Containing Drugs Including Other 5-HT1B/1D Agonists

Ergot-containing drugs have been reported to cause prolonged vasospastic reactions. Because these effects may be additive, use of ergotamine-containing or ergot-type medications (like dihydroergotamine [DHE] or methysergide) and RELPAX within 24 hours of each other is contraindicated. Concomitant use of other 5-HT1 agonists within 24 hours of RELPAX treatment is contraindicated [see Contraindications (4)].

7.2 CYP3A4 Inhibitors

Potent CYP3A4 inhibitors significantly increase the exposure of RELPAX. RELPAX should not be used within at least 72 hours of treatment with potent CYP3A4 inhibitors [see Contraindications (4) and Clinical Pharmacology (12.3)].

7.3 Selective Serotonin Reuptake Inhibitors/Serotonin and Norepinephrine Reuptake Inhibitors and Serotonin Syndrome

Cases of serotonin syndrome have been reported during co-administration of triptans and SSRIs, SNRIs, TCAs and MAO inhibitors [see Warnings and Precautions (5.7)].

8 USE IN SPECIFIC POPULATIONS

8.1 Pregnancy

Risk Summary

Available human data on the use of RELPAX in pregnant women are not sufficient to draw conclusions about drug-associated risk for major birth defects and miscarriage. In animal studies, oral administration of eletriptan during pregnancy or throughout pregnancy and lactation was associated with developmental toxicity (decreased fetal and pup weights, increased incidences of fetal structural abnormalities, decreased pup viability) at clinically-relevant doses [see Data].

In the U.S. general population, the estimated background risk of major birth defects and miscarriage in clinically recognized pregnancies is 2% to 4% and 15% to 20%, respectively. The reported rate of major birth defects among deliveries to women with migraine ranged from 2.2% to 2.9% and the reported rate of miscarriage was 17%, which were similar to rates reported in women without migraine.

Clinical Considerations

Disease-Associated Maternal and/or Embryo/Fetal Risk

Several studies have suggested that women with migraine may be at increased risk of preeclampsia and gestational hypertension during pregnancy.

Data

Human Data

A study using linked data from the Medical Birth Registry of Norway to the Norwegian Prescription Database compared pregnancy outcomes in women who redeemed prescriptions for triptans during pregnancy, as well as a migraine disease comparison group who redeemed prescriptions for triptans before pregnancy only. Of the 189 women who redeemed prescriptions for eletriptan during the first trimester, 4 (2.1%) had infants with major congenital malformations, while for the 174 women who redeemed prescriptions for eletriptan before, but not during, pregnancy, 11 (6.3%) had infants with major congenital malformations. Methodological limitations of this study, including small size of the eletriptan population and infrequent events, do not allow for thorough characterization of risk.

Animal Data

When pregnant rats were administered eletriptan (0, 10, 30, or 100 mg/kg/day) during the period of organogenesis, fetal weights were decreased and the incidences of vertebral and sternebral variations were increased at 100 mg/kg/day (approximately 12 times the maximum recommended human dose [MRHD] of 80 mg/day on a mg/m^2 basis). The 30 and 100 mg/kg/day doses were also maternally toxic, as evidenced by decreased maternal body weight gain during gestation. The no-effect dose for adverse effects on embryofetal development in rats was 30 mg/kg/day, which is approximately 4 times the MRHD on a mg/m^2 basis.

When eletriptan (0, 5, 10, or 50 mg/kg/day) was orally administered to pregnant rabbits throughout organogenesis, fetal weights were decreased at 50 mg/kg/day. The incidences of fused sternebrae and vena cava deviations were increased at all doses. Maternal toxicity was not evident at any dose. A no-effect dose for adverse effects on embryofetal development in rabbits was not established; the lowest dose tested (5 mg/kg/day) is similar to the MRHD on a mg/m^2 basis.

Oral administration of eletriptan (0, 5, 15, or 50 mg/kg/day) to female rats throughout pregnancy and lactation resulted in a decrease in offspring viability and body weight at the highest dose tested. The no-effect dose for adverse effects on pre- and postnatal development in rats (15 mg/kg/day) is approximately 2 times the MRHD on a mg/m^2 basis.

8.2 Lactation

Risk Summary

Eletriptan is excreted in human milk. There are no data on the effects of eletriptan on the breastfed infant or the effects of eletriptan on milk production.

The developmental and health benefits of breastfeeding should be considered along with the mother’s clinical need for RELPAX and any potential adverse effects on the breastfed child from RELPAX or from the underlying maternal condition. Infant exposure can be minimized by avoiding breastfeeding for 24 hours after treatment.

8.4 Pediatric Use

Safety and effectiveness in pediatric patients have not been established.

The efficacy of RELPAX Tablets (40 mg) in patients 11-17 was not established in a randomized, placebo-controlled trial of 274 adolescent migraineurs [see Clinical Studies (14)]. Adverse reactions observed were similar in nature to those reported in clinical trials in adults. Postmarketing experience with other triptans includes a limited number of reports that describe pediatric patients who have experienced clinically serious adverse reactions that are similar in nature to those reported rarely in adults. Long-term safety of eletriptan was studied in 76 adolescent patients who received treatment for up to one year. A similar profile of adverse reactions to that of adults was observed. The long-term safety of eletriptan in pediatric patients has not been established.

8.5 Geriatric Use

Blood pressure was increased to a greater extent in elderly subjects than in young subjects. The pharmacokinetic disposition of eletriptan in the elderly is similar to that seen in younger adults [see Clinical Pharmacology (12.3)]. In clinical trials, there were no apparent differences in efficacy or the incidence of adverse reactions between patients under 65 years of age and those 65 and above.

8.6 Hepatic Impairment

The effect of severe hepatic impairment on RELPAX metabolism has not been evaluated. RELPAX is not recommended for use in patients with severe hepatic impairment [see Clinical Pharmacology (12.3)].

10 OVERDOSAGE

The elimination half-life of eletriptan is about 4 hours [see Clinical Pharmacology (12.3)], therefore monitoring of patients after overdose with eletriptan should continue for at least 20 hours or longer while symptoms or signs persist.

There is no specific antidote to eletriptan.

It is unknown what effect hemodialysis or peritoneal dialysis has on the serum concentration of eletriptan.

11 DESCRIPTION

RELPAX (eletriptan hydrobromide) tablets contain eletriptan hydrobromide, which is a selective 5-hydroxytryptamine 1B/1D (5-HT1B/1D) receptor agonist. Eletriptan hydrobromide is chemically designated as (R)-3-[(1-Methyl-2-pyrrolidinyl)methyl]-5-[2-(phenylsulfonyl)ethyl]-1H-indole monohydrobromide, and it has the following chemical structure:

The empirical formula is C22H26N2O2S . HBr, representing a molecular weight of 463.43. Eletriptan hydrobromide is a white to light pale colored powder that is readily soluble in water.

Each RELPAX Tablet for oral administration contains 24.2 or 48.5 mg of eletriptan hydrobromide equivalent to 20 mg or 40 mg of eletriptan, respectively. Each tablet also contains the inactive ingredients croscarmellose sodium, FD&C Yellow No. 6 Aluminum Lake, hypromellose, lactose monohydrate, magnesium stearate, microcrystalline cellulose, titanium dioxide, and triacetin USP.

12 CLINICAL PHARMACOLOGY

12.1 Mechanism of Action

Eletriptan binds with high affinity to 5-HT1B, 5-HT1D and 5-HT1F receptors, has modest affinity for 5-HT1A, 5-HT1E, 5-HT2B and 5-HT7 receptors.

Migraines are likely due to local cranial vasodilatation and/or to the release of sensory neuropeptides (vasoactive intestinal peptide, substance P and calcitonin gene-related peptide) through nerve endings in the trigeminal system. The therapeutic activity of RELPAX for the treatment of migraine headache is thought to be due to the agonist effects at the 5-HT1B/1D receptors on intracranial blood vessels (including the arterio-venous anastomoses) and sensory nerves of the trigeminal system which result in cranial vessel constriction and inhibition of pro-inflammatory neuropeptide release.

12.3 Pharmacokinetics

Absorption

Eletriptan is well absorbed after oral administration with peak plasma levels occurring approximately 1.5 hours after dosing to healthy subjects. In patients with moderate to severe migraine, the median Tmax is 2.0 hours. The mean absolute bioavailability of eletriptan is approximately 50%. The oral pharmacokinetics are slightly more than dose-proportional over the clinical dose range. The AUC and Cmax of eletriptan are increased by approximately 20 to 30% following oral administration with a high fat meal. RELPAX can be taken with or without food.

Distribution

The volume of distribution of eletriptan following IV administration is 138L. Plasma protein binding is moderate and approximately 85%.

Metabolism

The N-demethylated metabolite of eletriptan is the only known active metabolite. This metabolite causes vasoconstriction similar to eletriptan in animal models. Though the half-life of the metabolite is estimated to be about 13 hours, the plasma concentration of the N-demethylated metabolite is 10-20% of parent drug and is unlikely to contribute significantly to the overall effect of the parent compound.

In vitro studies indicate that eletriptan is primarily metabolized by cytochrome P-450 enzyme CYP3A4 [see Contraindications (4) and Drug Interactions (7.2)].

Elimination

The terminal elimination half-life of eletriptan is approximately 4 hours. Mean renal clearance (CLR) following oral administration is approximately 3.9 L/h. Non-renal clearance accounts for about 90% of the total clearance.

Specific Populations

Age

The pharmacokinetics of eletriptan are generally unaffected by age. Blood pressure was increased to a greater extent in elderly subjects than in young subjects [see Use in Specific Populations (8.5)]. The pharmacokinetic disposition of eletriptan in the elderly is similar to that seen in younger adults.

There is a statistically significant increased half-life (from about 4.4 hours to 5.7 hours) between elderly (65 to 93 years of age) and younger adult subjects (18 to 45 years of age) [see Use in Specific Populations (8.5)].

Gender

The pharmacokinetics of eletriptan are unaffected by gender.

Race

A comparison of pharmacokinetic studies run in western countries with those run in Japan has indicated an approximate 35% reduction in the exposure of eletriptan in Japanese male volunteers compared to western males. Population pharmacokinetic analysis of two clinical studies indicates no evidence of pharmacokinetic differences between Caucasians and non-Caucasian patients.

Menstrual Cycle

In a study of 16 healthy females, the pharmacokinetics of eletriptan remained consistent throughout the phases of the menstrual cycle.

Renal Impairment

There was no significant change in clearance observed in subjects with mild, moderate or severe renal impairment, though blood pressure elevations were observed in this population [see Warnings and Precautions (5.8)].

Hepatic Impairment

Subjects with mild or moderate hepatic impairment demonstrated an increase in both AUC (34%) and half-life. The Cmax was increased by 18%. No dose adjustment is necessary in subjects with mild or moderate hepatic impairment. The effects of severe hepatic impairment on eletriptan metabolism have not been evaluated [see Use in Specific Populations (8.6)].

Drug Interaction Studies

CYP3A4 Inhibitors

In vitro studies have shown that eletriptan is metabolized by the CYP3A4 enzyme. A clinical study demonstrated about a 3-fold increase in Cmax and about a 6-fold increase in the AUC of eletriptan when combined with ketoconazole. The half-life increased from 5 hours to 8 hours and the Tmax increased from 2.8 hours to 5.4 hours. Another clinical study demonstrated about a 2-fold increase in Cmax and about a 4-fold increase in AUC when erythromycin was co-administered with eletriptan. It has also been shown that co-administration of verapamil and eletriptan yields about a 2-fold increase in Cmax and about a 3-fold increase in AUC of eletriptan, and that co-administration of fluconazole and eletriptan yields about a 1.4-fold increase in Cmax and about a 2-fold increase in AUC of eletriptan.

RELPAX is contraindicated within at least 72 hours of treatment with the following potent CYP3A4 inhibitors: ketoconazole, itraconazole, nefazodone, troleandomycin, clarithromycin, ritonavir and nelfinavir. RELPAX should not be used within 72 hours with drugs that have demonstrated potent CYP3A4 inhibition [see Contraindications (4)].

Propranolol

The Cmax and AUC of eletriptan were increased by 10 and 33%, respectively, in the presence of propranolol. No interactive increases in blood pressure were observed. No dosage adjustment appears to be needed for patients taking propranolol.

The Effect of Eletriptan on Other Drugs

The effect of eletriptan on enzymes other than cytochrome P450 has not been investigated. In vitro human liver microsome studies suggest that eletriptan has little potential to inhibit CYP1A2, 2C9, 2E1 and 3A4 at concentrations up to 100 µM. While eletriptan has an effect on CYP2D6 at high concentration, this effect should not interfere with metabolism of other drugs when eletriptan is used at recommended doses. There is no in vitro or in vivo evidence that clinical doses of eletriptan will induce drug metabolizing enzymes. Therefore, eletriptan is unlikely to cause clinically important drug interactions mediated by these enzymes.

13 NONCLINICAL TOXICOLOGY

13.1 Carcinogenesis, Mutagenesis, Impairment of Fertility

Carcinogenesis

Eletriptan was administered to rats and mice in the diet for 104 weeks. In rats, the incidence of testicular interstitial cell adenomas was increased at the high dose of 75 mg/kg/day, but not at 15 mg/kg/day, a dose associated with plasma exposures (AUC) approximately 2 times that in humans at the MRHD of 80 mg/day. In mice, the incidence of hepatocellular adenomas was increased at the high dose of 400 mg/kg/day, but not a dose of 90 mg/kg/day, associated with plasma AUC approximately 7 times that in humans at the MRHD.

Mutagenesis

Eletriptan was negative in in vitro (bacteria reverse mutation (Ames), mammalian cell gene mutation (CHO/HGPRT), chromosomal aberration assay in human lymphocytes) and in vivo (mouse micronucleus) assays.

Impairment of Fertility

In a fertility and early embryonic development study, eletriptan (50, 100, or 200 mg/kg/day) was orally administered to male and female rats prior to and throughout mating and continuing in females to implantation. Plasma exposures (AUC) were 4, 8 and 16 times in males and 7, 14 and 28 times in females, respectively, that in humans at the MRHD. Prolongation of the estrous cycle and decreases in the number of corpora lutea, implants, and viable fetuses per dam were observed at 200 mg/kg/day. Male fertility parameters were not affected.

14 CLINICAL STUDIES

The efficacy of RELPAX in the acute treatment of migraines was evaluated in eight randomized, double-blind placebo-controlled studies. All eight studies used 40 mg. Seven studies evaluated an 80 mg dose and two studies included a 20 mg dose.

In all eight studies, randomized patients treated their headaches as outpatients. Seven studies enrolled adults and one study enrolled adolescents (ages 11 to 17). Patients treated in the seven adult studies were predominantly female (85%) and Caucasian (94%) with a mean age of 40 years (range 18 to 78). In all studies, patients were instructed to treat a moderate to severe headache. Headache response, defined as a reduction in headache severity from moderate or severe pain to mild or no pain, was assessed up to 2 hours after dosing. Associated symptoms such as nausea, vomiting, photophobia and phonophobia were also assessed.

Maintenance of response was assessed for up to 24 hours post dose. In the adult studies, a second dose of RELPAX or other medication was allowed 2 to 24 hours after the initial treatment for both persistent and recurrent headaches. The incidence and time to use of these additional treatments were also recorded.

In the seven adult studies, the percentage of patients achieving headache response 2 hours after treatment was significantly greater among patients receiving RELPAX at all doses compared to those who received placebo. The 2-hour response rates from these controlled clinical studies are summarized in Table 2.

Table 2: Percentage of Patients with Headache Response (Mild or No Headache) 2 Hours Following Treatment
 | Placebo | RELPAX 20 mg | RELPAX 40 mg | RELPAX 80 mg
Study 1 | 23.8% (n=126) | 54.3% [p value < 0.05 vs placebo] (n=129) | 65.0% (n=117) | 77.1% (n=118)
Study 2 | 19.0% (n=232) | NA | 61.6% (n=430) | 64.6% (n=446)
Study 3 | 21.7% (n=276) | 47.3% (n=273) | 61.9% (n=281) | 58.6% (n=290)
Study 4 | 39.5% (n=86) | NA | 62.3% (n=175) | 70.0% (n=170)
Study 5 | 20.6% (n=102) | NA | 53.9% (n=206) | 67.9% (n=209)
Study 6 | 31.3% (n=80) | NA | 63.9% (n=169) | 66.9% (n=160)
Study 7 | 29.5% (n=122) | NA | 57.5% (n=492) | NA
NA - Not Applicable

Comparisons of the performance of different drugs based upon results obtained in different clinical trials are never reliable. Because studies are generally conducted at different times, with different samples of patients, by different investigators, employing different criteria and/or different interpretations of the same criteria, under different conditions (dose, dosing regimen, etc.), quantitative estimates of treatment response and the timing of response may be expected to vary considerably from study to study.

The estimated probability of achieving an initial headache response within 2 hours following treatment is depicted in Figure 1.

*Figure 1 shows the Kaplan-Meier plot of probability over time of obtaining headache response (no or mild pain) following treatment with eletriptan. The plot is based on 7 placebo-controlled, outpatient trials in adults providing evidence of efficacy (Studies 1 through 7). Patients not achieving headache response or taking additional treatment prior to 2 hours were censored at 2 hours.

For patients with migraine-associated photophobia, phonophobia, and nausea at baseline, there was a decreased incidence of these symptoms following administration of RELPAX as compared to placebo.

Two to 24 hours following the initial dose of study treatment, patients were allowed to use additional treatment for pain relief in the form of a second dose of study treatment or other medication. The estimated probability of taking a second dose or other medications for migraine over the 24 hours following the initial dose of study treatment is summarized in Figure 2.

*This Kaplan-Meier plot is based on data obtained in 7 placebo-controlled trials in adults (Studies 1 through 7). Patients were instructed to take a second dose of study medication as follows: a) in the event of no response at 2 hours (studies 2 and 4-7) or at 4 hours (study 3); b) in the event of headache recurrence within 24 hours (studies 2-7). Patients not using additional treatments were censored at 24 hours. The plot includes both patients who had headache response at 2 hours and those who had no response to the initial dose. It should be noted that the protocols did not allow re-medication within 2 hours post dose.

The efficacy of RELPAX was unaffected by the duration of attack, gender or age of the patient, relationship to menses, or concomitant use of estrogen replacement therapy/oral contraceptives or frequently used migraine prophylactic drugs.

In a single study in adolescents (n=274), there were no statistically significant differences between treatment groups. The headache response rate at 2 hours was 57% for both RELPAX 40 mg Tablets and placebo.

16 HOW SUPPLIED/STORAGE AND HANDLING

RELPAX Tablets containing 20 mg or 40 mg eletriptan (base) as the hydrobromide salt. RELPAX Tablets are orange, round, convex shaped, film-coated tablets with appropriate debossing.

They are supplied in the following strengths and package configurations:

RELPAX Tablets

Package Configuration | Tablet Strength; (mg) | NDC Code | Debossing
Carton of 6 tablets; One blister of 6 tablets in a carton. | 20 mg | 58151-367-56 | REP 20 on one side and VLE on the other side
Carton of 6 tablets; One blister of 6 tablets in a carton. | 40 mg | 58151-368-56 | REP 40 on one side and VLE on the other side
Carton of 12 tablets.; Two blisters of 6 tablets in each carton. | 40 mg | 58151-368-96 | REP 40 on one side and VLE on the other side

Store at 20°C to 25°C (68°F to 77°F); excursions permitted between 15°C to 30°C (59°F to 86°F) [see USP Controlled Room Temperature].

17 PATIENT COUNSELING INFORMATION

See FDA-Approved Patient Labeling (Patient Information)

Myocardial Ischemia and/or Infarction, Prinzmetal’s Angina, Other Vasospastic Reactions, and Cerebrovascular Events

Inform patients that RELPAX may cause serious cardiovascular adverse reactions such as myocardial infarction or stroke, which may result in hospitalization and even death. Although serious cardiovascular reactions can occur without warning symptoms, instruct patients to be alert for the signs and symptoms of chest pain, shortness of breath, weakness, slurring of speech, and instruct them to ask for medical advice when observing any indicative sign or symptoms. Instruct patients to seek medical advice if they have symptoms of other vasospastic reactions [see Warnings and Precautions (5.1, 5.2, 5.4, 5.5, and 5.8)].

Anaphylactic/Anaphylactoid Reactions

Inform patients that anaphylactic/anaphylactoid reactions have occurred in patients receiving RELPAX. Such reactions can be life-threatening or fatal. In general, anaphylactic reactions to drugs are more likely to occur in individuals with a history of sensitivity to multiple allergens [see Contraindications (4)].

Medication Overuse Headache

Inform patients that use of drugs to treat acute migraines for 10 or more days per month may lead to an exacerbation of headache, and encourage patients to record headache frequency and drug use (e.g., by keeping a headache diary) [see Warnings and Precautions (5.6)].

Serotonin Syndrome

Inform patients about the risk of serotonin syndrome with the use of RELPAX or other triptans, particularly during combined use with selective serotonin reuptake inhibitors (SSRIs) or serotonin and norepinephrine reuptake inhibitors (SNRIs) [see Warnings and Precautions (5.7) and Drug Interactions (7.3)].

Pregnancy

Advise patients to notify their healthcare provider if they become pregnant or intend to become pregnant during therapy [see Use in Specific Populations (8.1)].

Lactation

Inform patients to notify their healthcare provider if they are breastfeeding or plan to breastfeed [see Use in Specific Populations (8.2)].

Distributed by:
Viatris Specialty LLC
Morgantown, WV 26505 U.S.A.

© 2024 Viatris Inc.

RELPAX is a registered trademark of Viatris Specialty LLC, a Viatris Company.

UPJ:RLPX:R2

Patient Information

RELPAX® (REL - packs)

(eletriptan hydrobromide)

Tablets

Please read this information before you start taking RELPAX and each time you get a refill. There may be new information. This information does not take the place of talking with your doctor about your medical condition or your treatment.

What is the most important information I should know about RELPAX?

RELPAX can cause serious side effects, including:

Heart attack and other heart problems. Heart problems may lead to death.

Stop taking RELPAX and get emergency medical help right away if you have any of the following symptoms of a heart attack:

- discomfort in the center of your chest that lasts for more than a few minutes, or that goes away and comes back
- chest pain or chest discomfort that feels like an uncomfortable heavy pressure, squeezing, fullness, or pain
- pain or discomfort in your arms, back, neck, jaw, or stomach
- shortness of breath with or without chest discomfort
- breaking out in a cold sweat
- nausea or vomiting
- feeling lightheaded

RELPAX is not for people with risk factors for heart disease unless a heart exam is done and shows no problem. You have a higher risk for heart disease if you:

- have high blood pressure
- have high cholesterol levels
- smoke
- are overweight
- have diabetes
- have a family history of heart disease
- are a female who has gone through menopause
- are a male over age 40

Serotonin syndrome. Serotonin syndrome is a serious and life-threatening problem that can happen in people taking RELPAX, especially if RELPAX is taken with anti-depressant medicines called selective serotonin reuptake inhibitors (SSRIs) or serotonin and norepinephrine reuptake inhibitors (SNRIs).

Ask your doctor or pharmacist for a list of these medicines if you are not sure.

Call your doctor right away if you have any of the following symptoms of serotonin syndrome:

- mental changes such as seeing things that are not there (hallucinations), agitation, or coma
- fast heartbeat
- changes in blood pressure
- high body temperature
- tight muscles
- trouble walking
- nausea, vomiting, or diarrhea

What is RELPAX?

RELPAX is a prescription medicine used to treat acute migraine headaches with or without aura in adults.

RELPAX is for people who have been diagnosed with migraine headaches.

RELPAX is not used to prevent or decrease the number of migraine headaches you have.

It is not known if RELPAX is safe and effective to treat cluster headaches.

It is not known if RELPAX is safe and effective in children.

Who should not take RELPAX?

Do not take RELPAX if you:

- have heart problems or a history of heart problems
- have or have had a stroke or problems with your blood circulation
- have hemiplegic or basilar migraines. If you are not sure if you have these types of migraines, ask your doctor.
- have narrowing of the blood vessels in your legs, arms, stomach, or kidney (peripheral vascular disease)
- have ischemic bowel disease
- have uncontrolled high blood pressure
- have taken any of the following medicines in the last 24 hours:
  - other "triptans" or triptan combination products such as:

- almotriptan (Axert®)
- frovatriptan (Frova®)
- naratriptan (Amerge®)
- rizatriptan (Maxalt®)
- sumatriptan (Imitrex®)

- sumatriptan and naproxen sodium, (Treximet®)
- zolmitriptan (Zomig®)

  - ergotamines such as:

- Bellergal-S®
- Cafergot®

- Ergomar®
- Wigraine®

  - dihydroergotamines such as:
    - D.H.E. 45® or Migranal® or methysergide (Sansert®)
- have taken the following medicines within the last 72 hours:

  - ketoconazole (Nizoral®)
  - itraconazole (Sporanox®)
  - nefazodone (Serzone®)
  - troleandomycin (TAO®)

- clarithromycin (Biaxin®)
- ritonavir (Norvir®)
- nelfinavir (Viracept®)

- are allergic to eletriptan or any of the ingredients in RELPAX. See the end of this leaflet for a complete list of ingredients in RELPAX.

What should I tell my doctor before taking RELPAX?

Before you take RELPAX, tell your doctor if you:

- have heart problems or family history of heart problems or stroke
- have high blood pressure
- have high cholesterol
- have diabetes
- smoke
- are overweight
- are a female who has gone through menopause
- have kidney problems
- have liver problems
- are pregnant or plan to become pregnant. It is not known if RELPAX will harm your unborn baby.
- are breastfeeding or plan to breastfeed. RELPAX passes into your breast milk and may harm your baby. Talk to your doctor about the best way to feed your baby if you take RELPAX.

Tell your doctor about all the medicines you take, including prescription and over-the-counter medicines, vitamins, and herbal supplements. Your doctor will decide if you can take RELPAX with your other medicines. RELPAX and other medicines may affect each other causing side effects.

Especially tell your doctor if you take anti-depressant medicines called:

- selective serotonin reuptake inhibitors (SSRIs)
- serotonin and norepinephrine reuptake inhibitors (SNRIs)

Ask your doctor or pharmacist for a list of these medicines if you are not sure.

Know the medicines you take. Keep a list of them to show your doctor or pharmacist when you get a new medicine.

How should I take RELPAX?

- Take RELPAX exactly as your doctor tells you to take it.
- Your doctor will tell you how much RELPAX to take and when to take it.
- Your doctor may change your dose if needed. Do not change your dose without first talking to your doctor.
- Take 1 RELPAX tablet as soon as you feel a migraine coming on.
- If you do not get any relief after your first RELPAX tablet, do not take a second tablet without first talking with your doctor.
- If your headache comes back or you only get some relief from your headache, you can take a second tablet 2 hours after the first tablet.
- Do not take more than a total of 80 mg of RELPAX tablets in a 24-hour period.
- If you take too much RELPAX, call your doctor or go to the nearest hospital emergency room right away.
- You should write down when you have headaches and when you take RELPAX so you can talk to your doctor about how well RELPAX is working for you.

What should I avoid while taking RELPAX?

RELPAX can cause dizziness, weakness, or drowsiness. If you have these symptoms, do not drive a car, use machinery, or do anything where you need to be alert.

What are the possible side effects of RELPAX?

RELPAX may cause serious side effects. See "What is the most important information I should know about RELPAX?"

These serious side effects include:

- changes in color or sensation in your fingers and toes (Raynaud's syndrome)
- stomach and intestinal problems (gastrointestinal and colonic ischemic events). Symptoms of gastrointestinal and colonic ischemic events include:
  - sudden or severe stomach pain
  - stomach pain after meals
  - weight loss
  - nausea or vomiting
  - constipation or diarrhea
  - bloody diarrhea
  - fever
- problems with blood circulation to your legs and feet (peripheral vascular ischemia). Symptoms of peripheral vascular ischemia include:
  - cramping and pain in your legs or hips
  - feeling of heaviness or tightness in your leg muscles
  - burning or aching pain in your feet or toes while resting
  - numbness, tingling, or weakness in your legs
  - cold feeling or color changes in 1 or both legs or feet
- medication overuse headaches. Some people who take too many RELPAX may have worse headaches (medication overuse headache). If your headaches get worse, your doctor may decide to stop your treatment with RELPAX.

The most common side effects of RELPAX include:

- dizziness
- nausea
- weakness
- tiredness
- drowsiness

Tell your doctor if you have any side effect that bothers you or that does not go away. These are not all the possible side effects of RELPAX. For more information, ask your doctor or pharmacist.

Call your doctor for medical advice about side effects. You may report side effects to the FDA at 1-800-FDA-1088.

How should I store RELPAX?

• Store RELPAX at room temperature between 68°F to 77°F (20°C to 25°C).

General information about the safe and effective use of RELPAX

Medicines are sometimes prescribed for conditions that are not mentioned in patient information leaflets. Do not use RELPAX for a condition for which it was not prescribed. Do not give RELPAX to other people, even if they have the same symptoms you have. It may harm them.

This Patient Information summarizes the most important information about RELPAX. If you would like more information about RELPAX, talk with your doctor. You can ask your doctor or pharmacist for information on RELPAX that is written for health professionals.

For more information, call Viatris at 1-877-446-3679 (1-877-4-INFO-RX).

What are the ingredients in RELPAX?

Active ingredient: eletriptan hydrobromide

Inactive ingredients: croscarmellose sodium, FD&C Yellow No. 6 Aluminum Lake, hypromellose, lactose monohydrate, magnesium stearate, microcrystalline cellulose, titanium dioxide, and triacetin.

Distributed by:
Viatris Specialty LLC
Morgantown, WV 26505 U.S.A.

© 2024 Viatris Inc.

RELPAX is a registered trademark of Viatris Specialty LLC, a Viatris Company.

The brands listed are trademarks of their respective owners.

This Patient Information has been approved by the U.S. Food and Drug Administration.

UPJ:PL:RLPX:R2

Revised: 1/2024

PRINCIPAL DISPLAY PANEL - 20 mg

20mg*

NDC 58151-367-56

RELPAX®
(eletriptan HBr)

6 tablets
1 card x six 20 mg tablets
Rx only

Store at 20°C to 25°C (68°F to 77°F);
excursions permitted between
15°C to 30°C (59°F to 86°F)
[see USP Controlled Room Temperature].

DOSAGE AND USE
See accompanying prescribing information.

*Each tablet contains eletriptan hydrobromide
equivalent to 20 mg eletriptan.

MADE IN ITALY

Distributed by:

Viatris Specialty LLC
Morgantown, WV 26505 U.S.A.
© 2023 Viatris Inc.

RELPAX is a registered trademark
of Viatris Specialty LLC,
a Viatris Company.

UPJ:367:6C:R1

PRINCIPAL DISPLAY PANEL - 40 mg

40mg*

NDC 58151-368-56

RELPAX®
(eletriptan HBr)

6 tablets
1 card x six 40 mg tablets
Rx only

Store at 20°C to 25°C (68°F to 77°F);
excursions permitted between
15°C to 30°C (59°F to 86°F)
[see USP Controlled Room Temperature].

DOSAGE AND USE
See accompanying prescribing information.

*Each tablet contains eletriptan hydrobromide
equivalent to 40 mg eletriptan.

MADE IN ITALY

Distributed by:

Viatris Specialty LLC
Morgantown, WV 26505 U.S.A.
© 2023 Viatris Inc.

RELPAX is a registered trademark
of Viatris Specialty LLC,
a Viatris Company.

UPJ:368:6C:R1